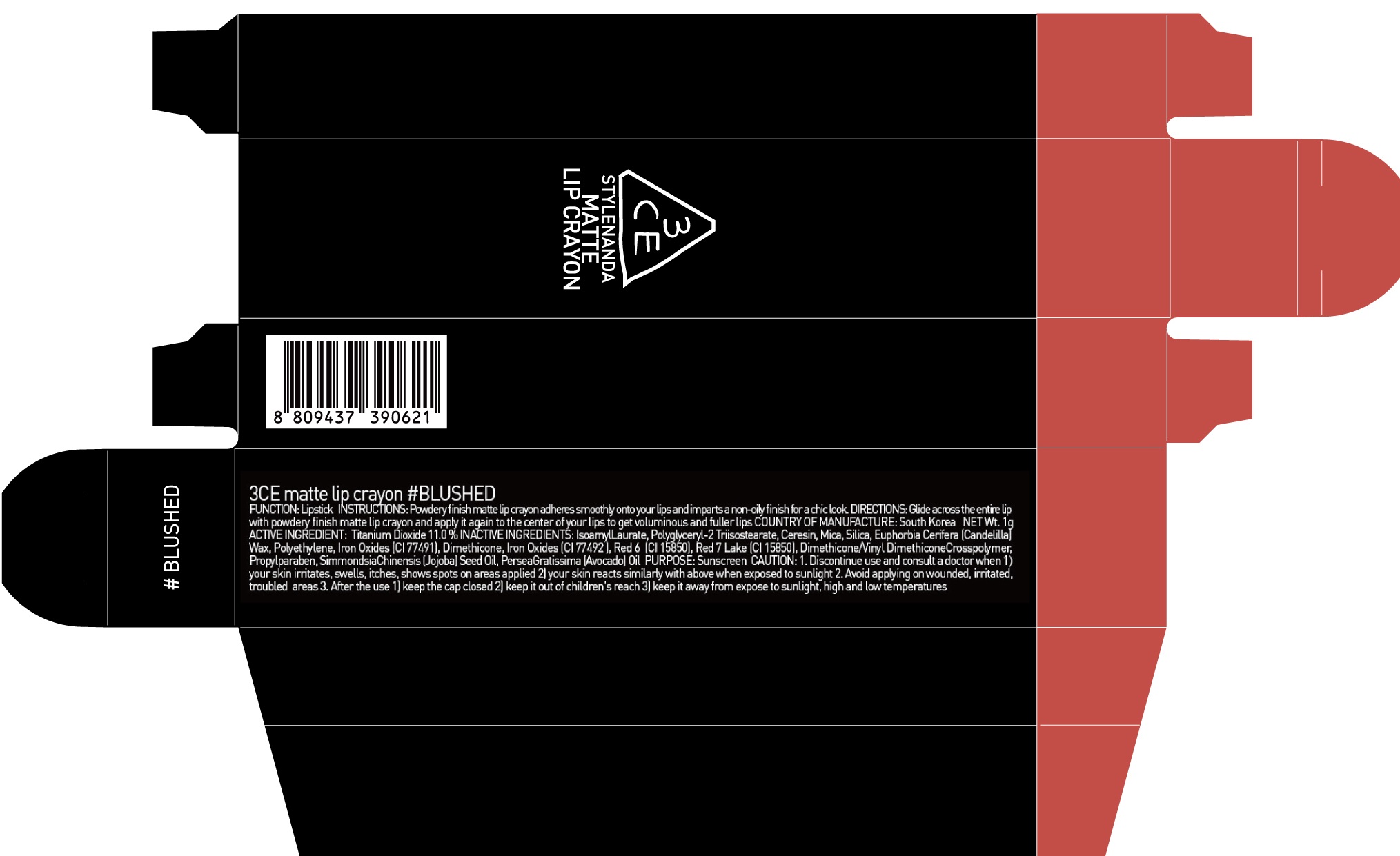 DRUG LABEL: 3CE MATTE LIP CRAYON BLUSHED
NDC: 60764-086 | Form: LIPSTICK
Manufacturer: Nanda Co., Ltd
Category: otc | Type: HUMAN OTC DRUG LABEL
Date: 20161011

ACTIVE INGREDIENTS: Titanium Dioxide 0.11 g/1 g
INACTIVE INGREDIENTS: Isoamyl Laurate; Ceresin

ACTIVE INGREDIENT

Active Ingredient: Titanium Dioxide 11.0%

INACTIVE INGREDIENT

Inactive Ingredients: Isoamyl Laurate, Polyglyceryl-2 Triisostearate, Ceresin, Mica, Silica, Euphorbia Cerifera (Candelilla) Wax, Polyethylene, Iron Oxides (CI 77491), Dimethicone, Iron Oxides (CI 77492), Red 6 (CI 15850), Red 7 Lake (CI 15850), Dimethicone/Vinyl DimethiconeCrosspolymer, Propylparaben, SimmondsiaChinensis (Jojoba) Seed Oil, PerseaGratissima (Avocado) Oil

PURPOSE

Purpose: Sunscreen

CAUTION

CAUTION: 1. Discontinue use and consult a doctor when - your skin irritates, swells, itches, shows spots on areas applied - your skin reacts similarly with above when exposed to sunlight 2. Avoid applying on wounded, irritated, troubled areas 3. After the use - keep the cap closed - keep it out of children's reach - keep it away from expose to sunlight, high and low temperatures

DESCRIPTION

INSTRUCTIONS: Powdery finish matte lip crayon adheres smoothly onto your lips and imparts a non-oily finish for a chic look.

Directions: Glide across the entire lip with powdery finish matte lip crayon and apply it again to the center of your lips to get voluminous and fuller lips